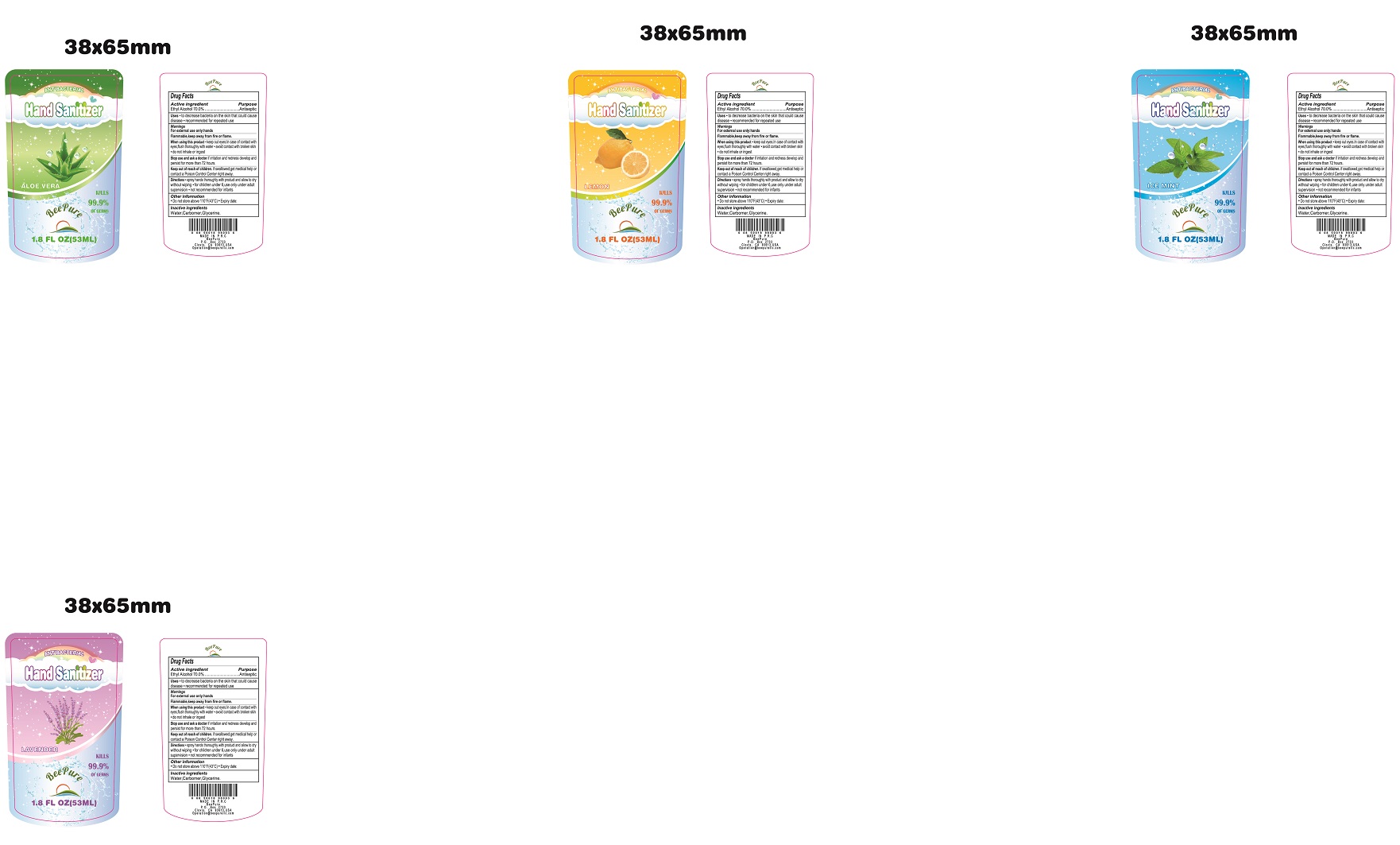 DRUG LABEL: Hand Sanitizer
NDC: 73946-004 | Form: GEL
Manufacturer: Yiwu Jiefei Daily Chemicals Co.,Ltd.
Category: otc | Type: HUMAN OTC DRUG LABEL
Date: 20200610

ACTIVE INGREDIENTS: ALCOHOL 70 mL/100 mL
INACTIVE INGREDIENTS: GLYCERIN; CARBOMER 934; WATER

73946-004 Hand Sanitizer Ethyl Alcohol 70%

Active Ingredient(s)

Isopropyl Alcohol 70%

Purpose

Antiseptic

Use

●to decrease bacteria on the skin that could cause disease
●recommended for repeated use

Warnings

For external use only: hands
Flammable, keep away from fire or flame.
When using this product●keep out eyes. In case of contact with
eyes, flush thoroughly with water●avoid contact with broken skin
●do not inhale or ingest
Stop use and ask a doctor if irritation and redness develop and
persist for more than 72 hours.

Keep out of reach of children. if swallowed, get medical help or
contact a Poison Control Center right away.

Directions

*spray hands thoroughly with product and allow to dry
without wiping●for children under 6, use only under adult supervision
●not recommended for infants

Inactive ingredients

Water,Carbomer,Glycerine.